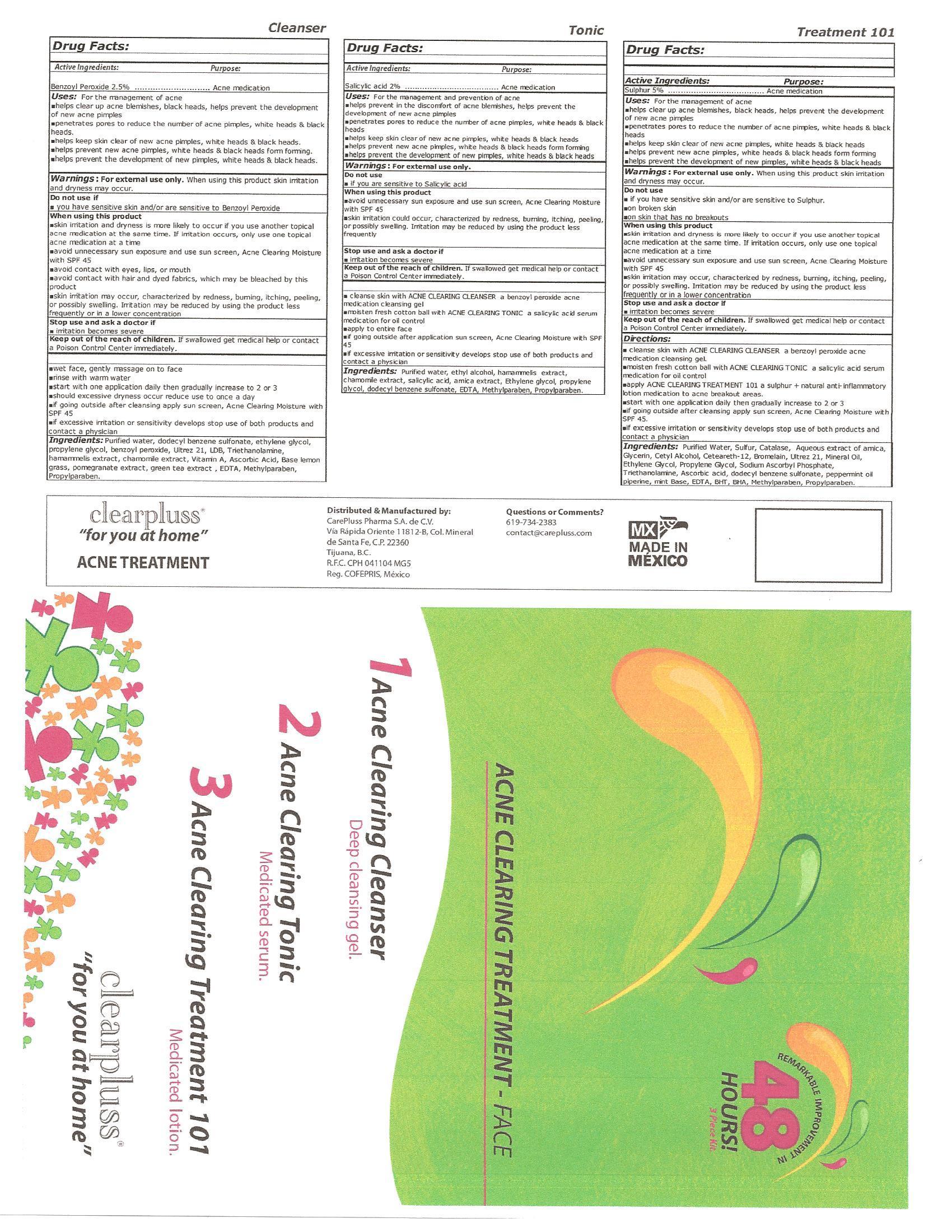 DRUG LABEL: Acne Clearning Treatment
NDC: 51439-007 | Form: LIQUID
Manufacturer: CarePluss Pharma S.A. de C.V.
Category: otc | Type: HUMAN OTC DRUG LABEL
Date: 20130320

ACTIVE INGREDIENTS: SULFUR .012 mg/.024 mg; BENZOYL PEROXIDE .006 mg/.024 mg; SALICYLIC ACID .0048 mg/.024 mg
INACTIVE INGREDIENTS: WATER; CATALINA; ARNICA MONTANA; GLYCERIN; CETYL ALCOHOL; CETEARETH-12; BROMELAINS; CARBOMER COPOLYMER TYPE A (ALLYL PENTAERYTHRITOL CROSSLINKED); MINERAL OIL; ETHYLENE GLYCOL; PROPYLENE GLYCOL; SODIUM ASCORBYL PHOSPHATE; TROLAMINE; ASCORBIC ACID; DODECYLBENZENESULFONIC ACID; PEPPERMINT OIL; PIPERINE; MINT; EDETIC ACID; BUTYLATED HYDROXYTOLUENE; METHYLPARABEN; PROPYLPARABEN; VITAMIN A; POMEGRANATE; GREEN TEA LEAF

Active Ingredient....................................Purpose
Sulphur 5%...............................................Acne medication
Benzoyl Peroxide 2.5%...............................Acme medication
Salicylic acid 2%........................................Acne medication

PURPOSE

Uses:For the management of acne

- helps clear up acne blemishes, black heads, helps prevent the development of new acne pimples
- penetrates pores to reduce the number of acne pimples, white heads and black heads
- help keep skin clear of new acne pimples, white heads and black heads
- helps prevent new acne pimples, white heads and black heads from forming
- help prevent the development of new pimples, white heads and black heads

Warnings: For external use only.
Do not use

- if you have sensitive skin and/or are sensitive to [active ingredient]

When using this product

- skin irritation and dryness is more likely to occur if you use another topical acne medication at the same time. If irritation occurs, only use one topical acne medication at a time
- avoid unnecessary sun exposure and use sun screen, Acne Clearing Moisture with SPF 45
- skin irritation may occur, characterized by redness, burning, itching, peeling, and possibly swelling. Irritation may be reduced by using the product less frequently or in a lower concentration

Stop use and ask a doctor if
irritation becomes severe

Keep out of reach of children.If swallowed get medical help or contact a Poison Control center immediately.

Directions:

1. Acne Clearing Cleanser
2. Acne Clearing Tonic
3. Acne Clearing Treatment 101

INACTIVE INGREDIENT

Ingredients: Purified Water, Ethyl Alcohol, Hamammelis Extract, Chamomile Extract, Salicyl Alcohol, Ethhylene Glycol, Propylene Glycol, Dodecyl Benzene Sulfonate, EDTA, Methylparaben, Propylparaben. Purified Water, Sulfer, Catalase, Aqueous extract of arnica, Glycerin, Cetyl Alcohol, Ceteareth-12, Bromelain, Ultrez 21, Mineral Oil, Ethhylene Glycol, Propylene Glycol, Sodium Ascorbyl Phosphate, Triethanolamine, Ascorbic Acid, Dodecyl Benzene Sulfonate, Peppermint oil, Piperine, Mint Base, EDTA, BHT, BHA, Methylparaben, Propylparaben.Purified Water, Sulfer, Catalase, Aqueous extract of arnica, Glycerin, Cetyl Alcohol, Ceteareth-12, Bromelain, Ultrez 21, Mineral Oil, Ethhylene Glycol, Propylene Glycol, Sodium Ascorbyl Phosphate, Triethanolamine, Ascorbic Acid, Dodecyl Benzene Sulfonate, Peppermint oil, Piperine, Mint Base, EDTA, BHT, BHA, Methylparaben, Propylparaben.

DOSAGE AND ADMINISTRATION

Three Bottles

1. Acne Clearing Cleanser 240 mL
2. Acne Clearing Tonic 120 mL
3. Acne Clearing Treatment 101 60 mL

PACKAGE LABEL

Acne Clearing Treatment - FACE